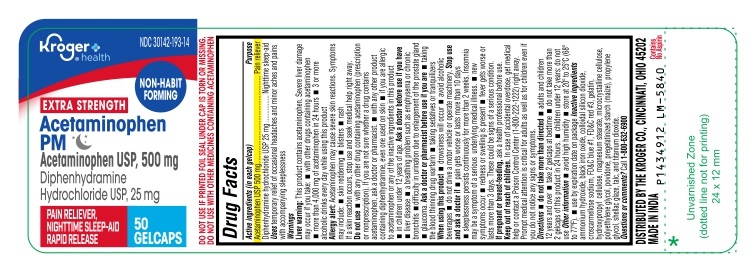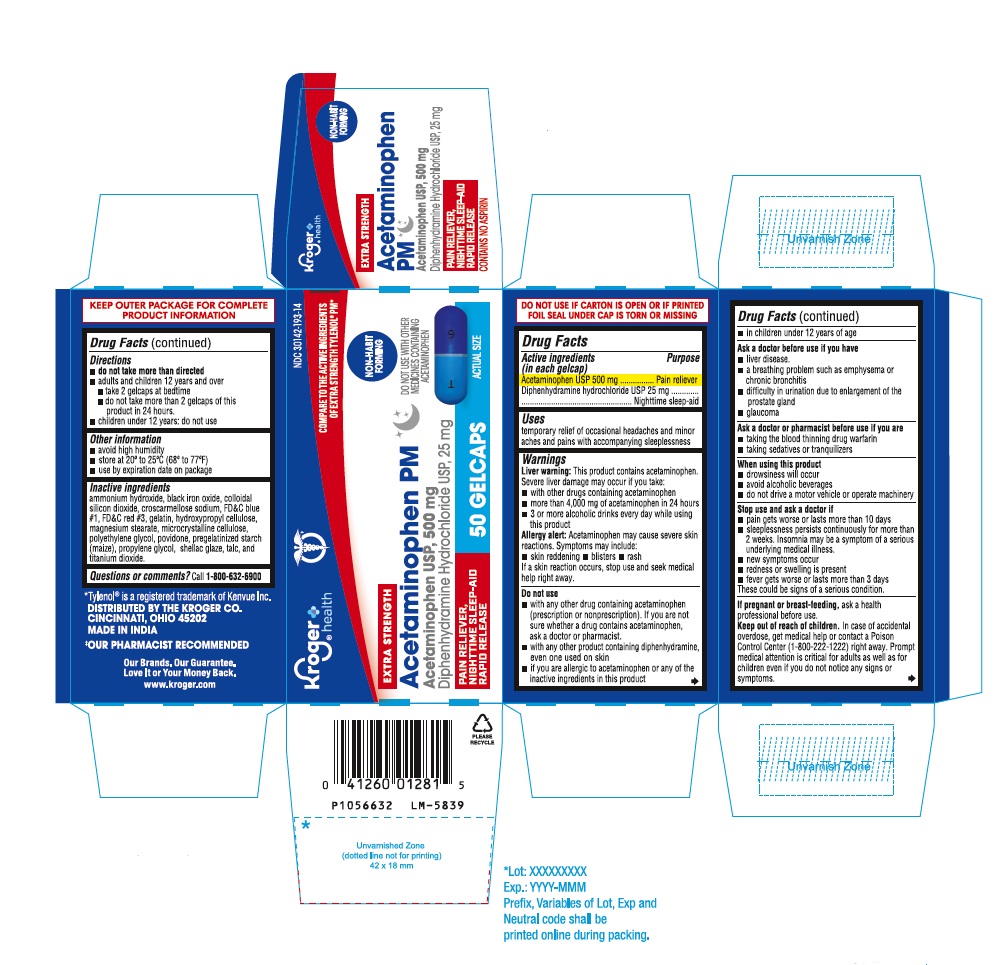 DRUG LABEL: Acetaminophen and Diphenhydramine hydrochloride
NDC: 30142-193 | Form: TABLET
Manufacturer: KROGER COMPANY
Category: otc | Type: Human OTC Drug Label
Date: 20240910

ACTIVE INGREDIENTS: ACETAMINOPHEN 500 mg/1 1; DIPHENHYDRAMINE HYDROCHLORIDE 25 mg/1 1
INACTIVE INGREDIENTS: AMMONIA; FERROSOFERRIC OXIDE; SILICON DIOXIDE; CROSCARMELLOSE SODIUM; FD&C BLUE NO. 1; FD&C RED NO. 3; GELATIN, UNSPECIFIED; HYDROXYPROPYL CELLULOSE (110000 WAMW); MAGNESIUM STEARATE; MICROCRYSTALLINE CELLULOSE 101; MICROCRYSTALLINE CELLULOSE 102; POLYETHYLENE GLYCOL 4000; POVIDONE K90; STARCH, CORN; PROPYLENE GLYCOL; SHELLAC; TALC; TITANIUM DIOXIDE

Drug Facts

Active ingredients (in each gelcap)
Acetaminophen USP 500 mg
Diphenhydramine hydrochloride USP 25 mg

Purpose

Pain reliever
Nighttime sleep-aid

Uses

temporary relief of occasional headaches and minor aches and pains with accompanying sleeplessness

Warnings

Liver warning: This product contains acetaminophen.
Severe liver damage may occur if you take:

- with other drugs containing acetaminophen
- more than 4,000 mg of acetaminophen in 24 hours
- 3 or more alcoholic drinks every day while using this product

Allergy alert: Acetaminophen may cause severe skin reactions. Symptoms may include:

- skin reddening
- blisters
- rash

If a skin reaction occurs, stop use and seek medical help right away.

Do not use

- with any other drug containing acetaminophen (prescription or nonprescription). If you are not sure whether a drug contains acetaminophen, ask a doctor or pharmacist.
- with any other product containing diphenhydramine, even one used on skin
- if you are allergic to acetaminophen or any of the inactive ingredients in this product
- in children under 12 years of age

Ask a doctor before use if you have

- liver disease
- a breathing problem such as emphysema or chronic bronchitis
- difficulty in urination due to enlargement of the prostate gland
- glaucoma

Ask a doctor or pharmacist before use if you are

- taking the blood thinning drug warfarin
- taking sedatives or tranquilizers

When using this product

- drowsiness will occur
- avoid alcoholic beverages
- do not drive a motor vehicle or operate machinery

Stop use and ask a doctor if

- pain gets worse or lasts more than 10 days
- sleeplessness persists continuously for more than 2 weeks. Insomnia may be a symptom of serious underlying medical illness.
- new symptoms occur
- redness or swelling is present
- fever gets worse or lasts more than 3 days

These could be signs of a serious condition.

If pregnant or breast-feeding,

ask a health professional before use.

Keep out of reach of children.

In case of accidental overdose, get medical help or contact a Poison Control Center (1-800-222-1222) right away. Prompt medical attention is critical for adults as well as for children even if you do not notice any signs or symptoms.

Directions

- do not take more than directed
- adults and children 12 years and over
  - take 2 gelcaps at bedtime
  - do not take more than 2 gelcaps of this product in 24 hours.
- children under 12 years: do not use

Other information

- avoid high humidity
- store at 20º to 25°C (68º to 77°F)
- use by expiration date on package

Inactive ingredients

ammonium hydroxide, black iron oxide, colloidal silicon dioxide, croscarmellose sodium, FD&C blue #1, FD&C red #3, gelatin, hydroxypropyl cellulose, magnesium stearate, microcrystalline cellulose, polyethylene glycol, povidone, pregelatinized starch (maize), propylene glycol, shellac glaze, talc, and titanium dioxide.

Questions or comments?

Call 1-800-632-6900
DISTRIBUTED BY THE KROGER CO.
CINCINNATI, OHIO 45202
MADE IN INDIA
Code: TS/DRUGS/16/2014

PACKAGE LABEL-PRINCIPAL DISPLAY PANEL 500 mg / 25 mg (50 Caplets Bottle)

NDC 30142-193-14
Kroger®
health
NON-HABIT
FORMING
EXTRA STRENGTH
Acetaminophen
PM
Acetaminophen USP, 500 mg

Diphenhydramine
Hydrochloride USP, 25 mg
PAIN RELIEVER,
NIGHTTIME SLEEP-AID
RAPID RELEASE
50
GELCAPS

PACKAGE LABEL-PRINCIPAL DISPLAY PANEL 500 mg / 25 mg (50 Caplets Bottle Carton)

NDC 30142-193-14
Kroger®
health
COMPARE TO THE ACTIVE INGREDIENTS
OF EXTRA STRENGTH TYLENOL® PM*
NON-HABIT
FORMING
EXTRA STRENGTH
Acetaminophen PM
Acetaminophen USP, 500 mg
Diphenhydramine Hydrochloride USP, 25 mg
DO NOT USE WITH OTHER
MEDICINES CONTAINING
ACETAMINOPHEN
PAIN RELIEVER,
NIGHTTIME SLEEP-AID
RAPID RELEASE
50 GELCAPS ACTUAL SIZE